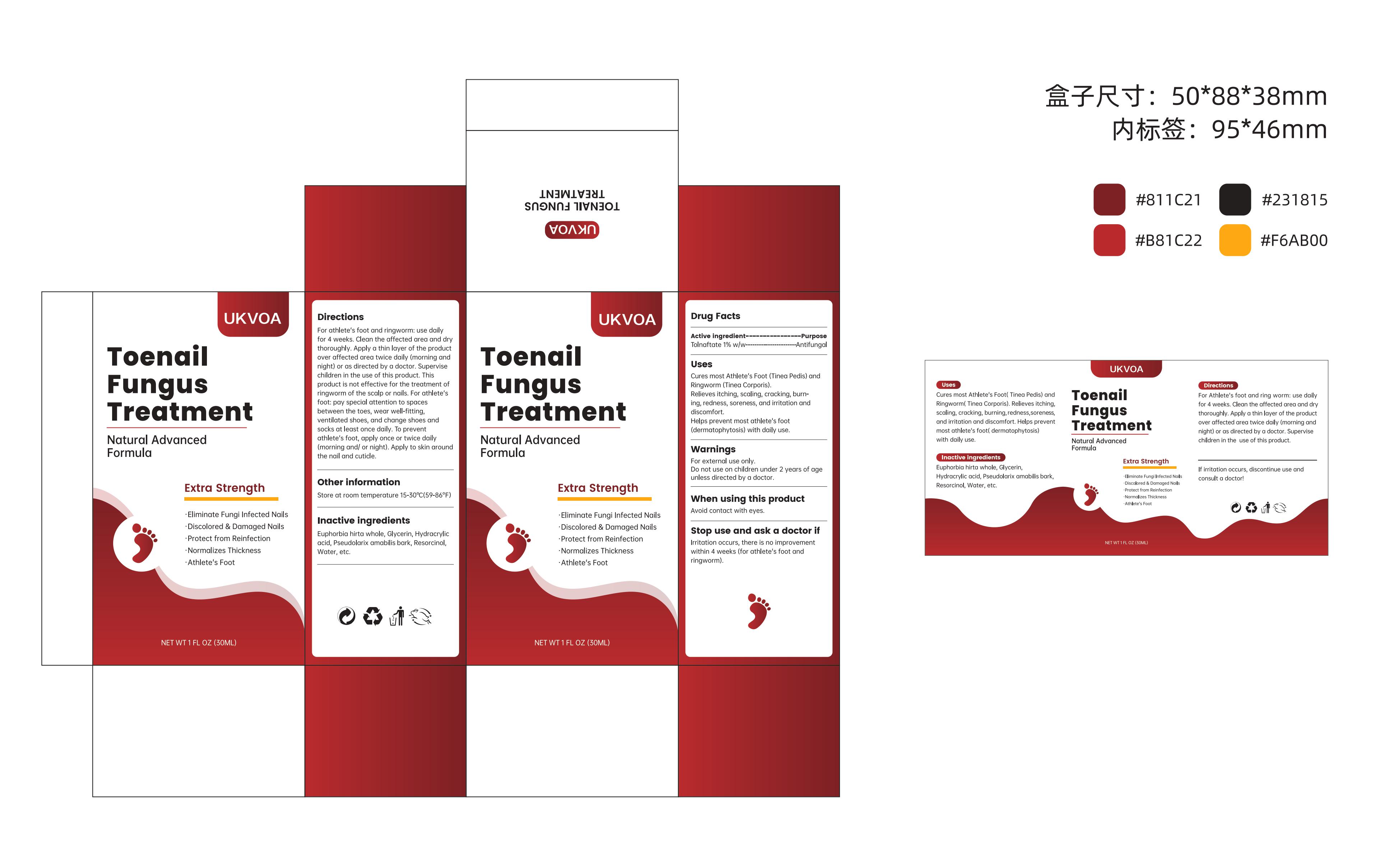 DRUG LABEL: UKVOA Toenail Fungus Treatment
NDC: 84867-012 | Form: LIQUID
Manufacturer: Jiashen International Trade Limited
Category: otc | Type: HUMAN OTC DRUG LABEL
Date: 20250216

ACTIVE INGREDIENTS: TOLNAFTATE 1 g/100 mL
INACTIVE INGREDIENTS: EUPHORBIA HIRTA WHOLE; GLYCERIN; HYDRACRYLIC ACID; RESORCINOL; WATER; PSEUDOLARIX AMABILIS BARK

Active Ingredient

Tolnaftate 1%

Purpose

Antifungal

Warnings

For external use only.Do not use on children under 2 years of ageunless directed by a
doctor.

Stop use

Stop use and ask a doctor ifirritation occurs, there is no improvementwithin 4 weeks
(for athlete's foot andringworm).

Do not use

If irritation occurs, discontinue useand consult a doctor!

Keep out of reach of children

lf swallowed, get medical help or contact aPoison Control Center(1-800-222-
1222)rightaway.

Directions for use

For athlete's foot and ringworm: use dailyfor 4 weeks. Clean the affected area and
drythoroughly. Apply a thin layer of the productover affected area twice daily (morning
andnight) or as directed by a doctor. Supervisechildren in the use of this product.
Thisproduct is not effective for the treatment ofringworm of the scalp or nails. For
athlete'sfoot: pay special attention to spacesbetween the toes, wear well-fitting.ventilated
shoes, and change shoes andsocks at least once daily. To preventathlete's foot, apply
once or twice daily(morning and/ or night). Apply to skin aroundthe nail and cuticle.

Dosage

For Athlete's foot and ring worm: use dailyfor 4 weeks. Clean the affected area and
drythoroughly. Apply a thin layer of the productover affected area twice daily (morning
andnight) or as directed by a doctor. Supervisechildren in the use of this product

When using

When using this product avoid contact with eyes.

Inactive ingredlents

Euphorbia hirta whole, Glycerin,Hydracrylic acid, Pseudolarix amabilisbark,Resorcinol,
Water,